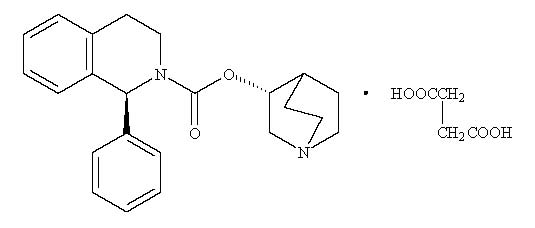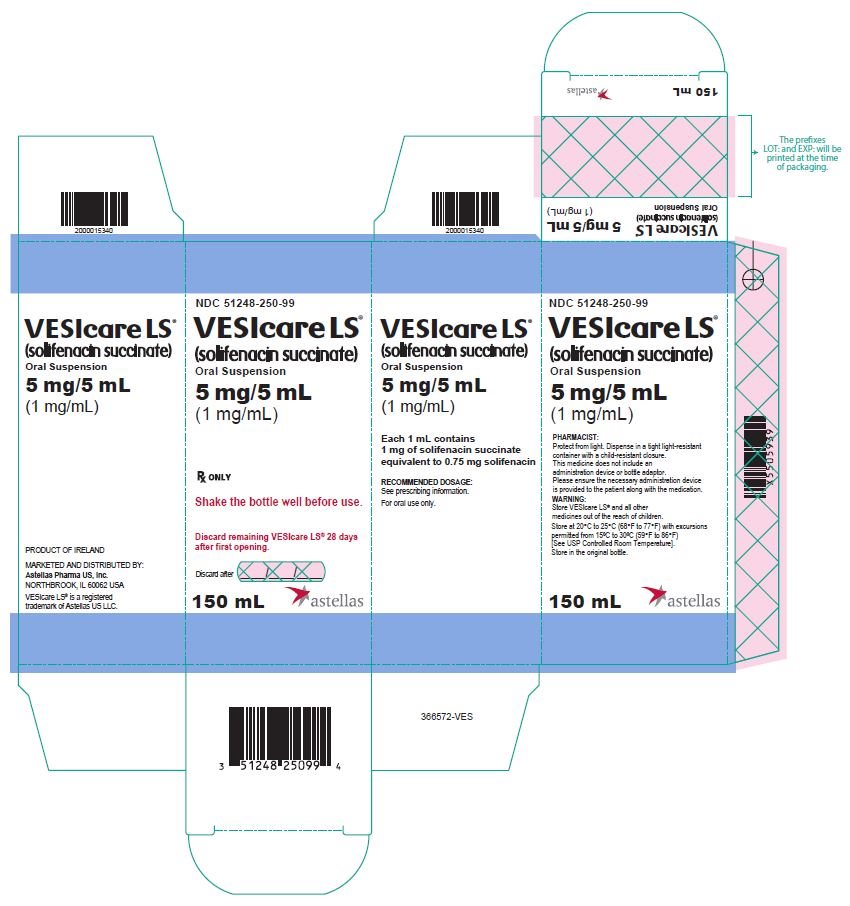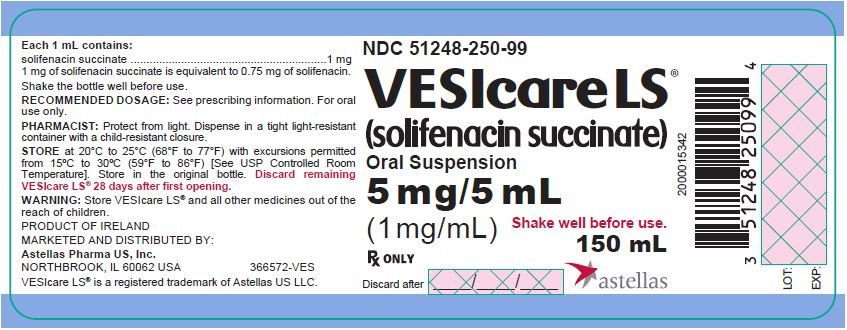 DRUG LABEL: VESIcare
NDC: 51248-250 | Form: SUSPENSION
Manufacturer: Astellas Pharma US, Inc.
Category: prescription | Type: HUMAN PRESCRIPTION DRUG LABEL
Date: 20221031

ACTIVE INGREDIENTS: SOLIFENACIN SUCCINATE 1 mg/1 mL
INACTIVE INGREDIENTS: POLACRILIN POTASSIUM; METHYLPARABEN; PROPYLPARABEN; PROPYLENE GLYCOL; DIMETHICONE; CARBOMER HOMOPOLYMER, UNSPECIFIED TYPE; XYLITOL; ACESULFAME POTASSIUM; SODIUM HYDROXIDE; WATER

HIGHLIGHTS OF PRESCRIBING INFORMATION

These highlights do not include all the information needed to use VESICARE LS safely and effectively. See full prescribing information for VESICARE LS.
VESICARE LS® (solifenacin succinate) oral suspension
Initial U.S. Approval: 2004

1 INDICATIONS AND USAGE

VESIcare LS is a muscarinic antagonist indicated for the treatment of neurogenic detrusor overactivity in pediatric patients aged 2 years and older. (1)

2 DOSAGE AND ADMINISTRATION

- The recommended once daily dose of VESIcare LS is based on patient weight, refer to Table 1. Dosing should be initiated at the recommended starting dose. Dosage may be titrated to the lowest effective dose but should not exceed the maximum recommended dose. (2.1)
- Instruct patients or their caregivers that patients should take VESIcare LS orally followed by liquid (e.g., water or milk).
- Do not exceed the recommended starting dose of VESIcare LS in patients with:
  - Severe renal impairment creatinine clearance < 30 mL/min/1.73 m^2. (2.2, 8.6)
  - Moderate hepatic impairment (Child-Pugh B). VESIcare LS is not recommended in patients with severe hepatic impairment (Child-Pugh C). (2.3, 8.7)
  - Concomitant use of strong CYP3A4 inhibitors. (2.4, 7.1)

3 DOSAGE FORMS AND STRENGTHS

Oral suspension: 5 mg/5 mL (1 mg/mL) of solifenacin succinate. (3)

4 CONTRAINDICATIONS

- Gastric retention. (4, 5.3)
- Uncontrolled narrow-angle glaucoma. (4, 5.5)
- Hypersensitivity to this product or any of its components. (4, 5.1, 6.2)

5 WARNINGS AND PRECAUTIONS

- Angioedema and Anaphylactic Reactions: Promptly discontinue VESIcare LS and provide appropriate therapy. (5.1)
- Urinary Retention: VESIcare LS is not recommended for use in patients with clinically significant bladder outlet obstruction in the absence of clean intermittent catherization. (5.2)
- Gastrointestinal Disorders: VESIcare LS is not recommended for use in patients with decreased gastrointestinal motility. (5.3)
- Central Nervous System Effects: Somnolence has been reported with solifenacin succinate. Advise patients not to drive or operate heavy machinery until they know how VESIcare LS affects them. (5.4)
- Controlled Narrow-Angle Glaucoma: Use VESIcare LS with caution in patients being treated for narrow-angle glaucoma. (5.5)
- QT Prolongation in Patients at High Risk of QT Prolongation:
  VESIcare LS is not recommended for use in patients at high risk of QT prolongation, including patients with a known history of QT prolongation and patients taking medications known to prolong the QT interval. (5.6)

6 ADVERSE REACTIONS

The most common adverse reactions (> 2%) were constipation, dry mouth and urinary tract infection. (6.1)

To report SUSPECTED ADVERSE REACTIONS, contact Astellas Pharma US, Inc. at 1-800-727-7003 or FDA at 1-800-FDA-1088 or www.fda.gov/medwatch.

7 DRUG INTERACTIONS

CYP3A4 Inhibitors: Do not exceed the recommended starting dose of VESIcare LS with concomitant use of strong CYP3A4 inhibitors. (7.1)

FULL PRESCRIBING INFORMATION

1 INDICATIONS AND USAGE

VESIcare LS® is indicated for the treatment of neurogenic detrusor overactivity (NDO) in pediatric patients aged 2 years and older.

2 DOSAGE AND ADMINISTRATION

2.1 Dosing Information

Dosing Information in Pediatric Patients Aged 2 Years and Older

The recommended starting and maximum VESIcare LS oral suspension doses are shown in mL in Table 1. VESIcare LS oral suspension has a concentration of 1 mg/1 mL. The recommended doses are weight-based and are administered once daily. After administration of the recommended starting dose, the dose may be increased to the lowest effective dose but should not exceed the maximum recommended dose.

Table 1: Once Daily Recommended Dosage According to Patient Body Weight
Weight range | Starting dose | Maximum dose
9 kg to 15 kg | 2 mL | 4 mL
greater than 15 kg to 30 kg | 3 mL | 5 mL
greater than 30 kg to 45 kg | 3 mL | 6 mL
greater than 45 kg to 60 kg | 4 mL | 8 mL
greater than 60 kg | 5 mL | 10 mL

Evaluate patients periodically for potential dose adjustment.

VESIcare LS oral suspension should be taken once daily. Instruct patients or their caregivers that patients should take VESIcare LS orally followed by liquid (e.g., water or milk). Instruct patients to take any missed doses as soon as they remember, unless more than 12 hours have passed since the missed dose. If more than 12 hours have passed, the missed dose can be skipped, and the next dose should be taken at the usual time.

2.2 Dosing Recommendations in Patients with Renal Impairment

Do not exceed the recommended VESIcare LS oral suspension starting dose in patients with severe renal impairment (CLcr < 30 mL/min/1.73 m^2) [see Use in Specific Populations (8.6)].

2.3 Dosing Recommendations in Patients with Hepatic Impairment

Do not exceed the recommended VESIcare LS oral suspension starting dose in patients with moderate hepatic impairment (Child-Pugh B). Do not use VESIcare LS in patients with severe hepatic impairment (Child-Pugh C) [see Use in Specific Populations (8.7)].

2.4 Dosing Recommendations in Patients Taking CYP3A4 Inhibitors

Do not exceed the recommended VESIcare LS oral suspension starting dose when VESIcare LS is administered with strong CYP3A4 inhibitors such as ketoconazole [see Drug Interactions (7.1)].

3 DOSAGE FORMS AND STRENGTHS

Oral Suspension: 5 mg/5 mL (1 mg/mL) of solifenacin succinate in a white to off-white colored suspension.

4 CONTRAINDICATIONS

VESIcare LS is contraindicated in patients:

- With gastric retention [see Warnings and Precautions (5.3)],
- With uncontrolled narrow-angle glaucoma [see Warnings and Precautions (5.5)], and
- Who have demonstrated hypersensitivity to solifenacin succinate or the inactive ingredients in VESIcare LS oral suspension. Reported adverse reactions have included anaphylaxis and angioedema [see Adverse Reactions (6.2)].

5 WARNINGS AND PRECAUTIONS

5.1 Angioedema and Anaphylactic Reactions

Angioedema of the face, lips, tongue, and/or larynx have been reported with solifenacin succinate. In some cases, angioedema occurred after the first dose, however, cases have been reported to occur hours after the first dose or after multiple doses. Anaphylactic reactions have also been reported in patients treated with solifenacin succinate. Angioedema associated with upper airway swelling and anaphylactic reactions may be life-threatening.

VESIcare LS oral suspension is contraindicated in patients with a known or suspected hypersensitivity to solifenacin succinate [see Contraindications (4)]. If involvement of the tongue, hypopharynx, or larynx occurs, promptly discontinue VESIcare LS oral suspension and provide appropriate therapy and/or measures necessary to ensure a patent airway.

5.2 Urinary Retention

The use of VESIcare LS oral suspension, like other antimuscarinic drugs, in patients with clinically significant bladder outlet obstruction may result in urinary retention. The use of VESIcare LS oral suspension is not recommended in patients with clinically significant bladder outflow obstruction in the absence of clean intermittent catheterization because of the risk of urinary retention.

5.3 Gastrointestinal Disorders

The use of VESIcare LS oral suspension, like other antimuscarinic drugs, in patients with conditions associated with decreased gastrointestinal motility may result in further decreased gastrointestinal motility. VESIcare LS oral suspension is contraindicated in patients with gastric retention [see Contraindications (4)]. The use of VESIcare LS oral suspension is not recommended in patients with conditions associated with decreased gastrointestinal motility.

5.4 Central Nervous System Effects

Solifenacin succinate is associated with antimuscarinic central nervous system (CNS) adverse reactions [see Adverse Reactions (6.2)]. A variety of CNS antimuscarinic adverse reactions have been reported, including headache, confusion, hallucinations, and somnolence. Monitor patients for signs of antimuscarinic CNS adverse reactions, particularly after beginning treatment or increasing the dose. Advise patients not to drive or operate heavy machinery until they know how VESIcare LS affects them. If a patient experiences antimuscarinic CNS adverse reactions, consider dose reduction or drug discontinuation.

5.5 Controlled Narrow-Angle Glaucoma

VESIcare LS should be used with caution in patients being treated for narrow-angle glaucoma [see Contraindications (4)].

5.6 QT Prolongation in Patients at High Risk of QT Prolongation

In a study of the effect of solifenacin succinate on the QT interval conducted in 76 healthy adult women [see Clinical Pharmacology (12.2)], solifenacin succinate 30 mg (three times the largest maximum recommended dose in pediatric patients) was associated with a mean increase in the Fridericia-corrected QT interval of 8 msec (90% CI, 4, 13). The QT prolonging effect appeared less with solifenacin succinate 10 mg than with solifenacin succinate 30 mg, and the effect of solifenacin succinate 30 mg did not appear as large as that of the positive control moxifloxacin at its therapeutic dose.

The use of VESIcare LS is not recommended in patients at high risk of QT prolongation, including patients with a known history of QT prolongation and patients who are taking medications known to prolong the QT interval.

6 ADVERSE REACTIONS

- Angioedema and Anaphylactic Reactions [see Warnings and Precautions (5.1)]
- Urinary Retention [see Warnings and Precautions (5.2)]
- Gastrointestinal Disorders [see Warnings and Precautions (5.3)]
- Central Nervous System Effects [see Warnings and Precautions (5.4)]
- QT Prolongation in Patients at High Risk of QT Prolongation [see Warnings and Precautions (5.6)]

6.1 Clinical Trials Experience

Because clinical trials are conducted under widely varying conditions, adverse reaction rates observed in the clinical trials of a drug cannot be directly compared to rates in the clinical trials of another drug and may not reflect the rates observed in practice.

The safety of VESIcare LS oral suspension was evaluated in two open-label trials (Studies 1 and 2) [see Clinical Studies (14)]. The two studies included 95 pediatric patients aged 2 to 17 years with neurogenic detrusor overactivity (NDO) who were 53% female, 58% White, 34% Asian and 2% Black. Treatment was initiated at the weight-based starting recommended dose and was titrated up or down in 2.5 mg increments over 12 weeks to the lowest effective dose (not to exceed the maximum recommended dose). Subsequent to the dose titration period, patients continued their optimized dose for a 40-week maintenance period (mean exposure duration 301 days, range 1 to 413 days).

The most commonly reported adverse reactions were constipation, dry mouth, urinary tract infection, abdominal pain, urinalysis bacterial test positive, and somnolence. The incidence of adverse reactions was similar between patients taking the starting recommended dose and patients taking the maximum recommended dose with the exception of constipation, which was reported, in 8.5% of patients taking the maximum recommended dose compared to 0% of patients taking the starting recommended dose.

Table 2 lists the adverse reactions reported in Studies 1 and 2 at an incidence equal to or greater than 1%.

Table 2: Adverse Reactions Reported in ≥ 1% of Neurogenic Detrusor Overactivity (NDO) Patients Aged 2 to 17 Years Taking VESIcare LS Oral Suspension in Studies 1 and 2
Adverse Reaction | Percentage (%) of Patients Reporting; Adverse Reactions; N=95
Constipation | 7.4
Dry mouth | 3.2
Urinary tract infection | 2.1
Abdominal pain | 1.1
Urinalysis bacterial test positive | 1.1
Somnolence | 1.1

Adverse reactions reported in ≥ 1% of solifenacin succinate-treated adult patients and at an incidence greater than in placebo-treated adult patients in clinical adult trials were:

Gastrointestinal disorders: dry mouth, constipation, nausea, dyspepsia, upper abdominal pain, vomiting

Infections and infestations: urinary tract infection, influenza, pharyngitis

Nervous system disorders: dizziness

Eye disorders: blurred vision, dry eyes

Renal and urinary disorders: urinary retention

General disorders and administration site conditions: lower limb edema, fatigue

Psychiatric disorders: depression

Respiratory, thoracic and mediastinal disorders: cough

Vascular disorders: hypertension

6.2 Postmarketing Experience

The following adverse reactions have been identified during post-approval use of solifenacin succinate. Because these reactions are reported voluntarily from a population of uncertain size, it is not always possible to reliably estimate their frequency or establish a causal relationship to drug exposure.

General disorders and administration site conditions: peripheral edema, hypersensitivity reactions (including angioedema with airway obstruction, rash, pruritus, urticaria, anaphylactic reaction);

Nervous system disorders: dizziness, headache, confusion, hallucinations, delirium, somnolence;

Cardiac disorders: QT prolongation, Torsade de Pointes, atrial fibrillation, tachycardia, palpitations;

Hepatobiliary disorders: liver disorders mostly characterized by abnormal liver function tests, AST (aspartate aminotransferase), ALT (alanine aminotransferase), GGT (gamma-glutamyl transferase);

Renal and urinary disorders: renal impairment, urinary retention;

Metabolism and nutrition disorders: decreased appetite, hyperkalemia;

Skin and subcutaneous tissue disorders: exfoliative dermatitis, erythema multiforme, dry skin;

Eye disorders: glaucoma;

Gastrointestinal disorders: gastroesophageal reflux disease, ileus, vomiting, abdominal pain, dysgeusia, sialadenitis;

Respiratory, thoracic and mediastinal disorders: dysphonia, nasal dryness;

Musculoskeletal and connective tissue disorders: muscular weakness.

7 DRUG INTERACTIONS

7.1 Strong CYP3A4 Inhibitors

Solifenacin is a substrate of CYP3A4. Concomitant use of ketoconazole, a strong CYP3A4 inhibitor, significantly increased the exposure of solifenacin [see Clinical Pharmacology (12.3)]. The dosage of VESIcare LS greater than the starting dose is not recommended when concomitantly used with strong CYP3A4 inhibitors [see Dosage and Administration (2.4)].

8 USE IN SPECIFIC POPULATIONS

8.1 Pregnancy

Risk Summary

There are no studies with the use of solifenacin succinate in pregnant women or adolescents to inform a drug-associated risk of major birth defects, miscarriages, or adverse maternal or fetal outcomes. No adverse developmental outcomes were observed in animal reproduction studies with oral administration of solifenacin succinate to pregnant mice during the period of organogenesis at a dose resulting in 1.2 times the systemic exposure at the maximum recommended human dose (MRHD) of 10 mg/day. However, administration of doses 3.6 times and greater than the MRHD during organogenesis produced maternal toxicity in the pregnant mice and resulted in developmental toxicity and reduced fetal body weights in offspring [see Data].

In the U.S. general population, the estimated background risk of major birth defects or miscarriage in clinically recognized pregnancies is 2-4% and 15-20%, respectively.

Data

Animal Data

Oral administration of ^14C-solifenacin succinate to pregnant mice resulted in the recovery of radiolabel in the fetus indicating that solifenacin-related product can cross the placental barrier. In pregnant mice, administration of solifenacin succinate at a dose of 250 mg/kg/day (7.9 times the systemic exposure at the MRHD of 10 mg), resulted in an increased incidence of cleft palate and increased maternal lethality. Administration of solifenacin succinate to pregnant mice during organogenesis at greater than or equal to 3.6 times (100 mg/kg/day and greater) the systemic exposure at the MRHD, resulted in reduced fetal body weights and reduced maternal body weight gain. No embryo-fetal toxicity or teratogenicity was observed in fetuses from pregnant mice treated with solifenacin succinate at a dose of 30 mg/kg/day (1.2 times the systemic exposure at the MRHD). Administration of solifenacin succinate to pregnant rats and rabbits at a dose of 50 mg/kg/day (< 1 times and 1.8 times the systemic exposure at the MRHD, respectively), resulted in no findings of embryo-fetal toxicity. Oral pre- and post-natal administration of solifenacin succinate at 100 mg/kg/day (3.6 times the systemic exposure at the MRHD) during the period of organogenesis through weaning, resulted in reduced peripartum and postnatal survival, reduced body weight gain by the pups, and delayed physical development (eye opening and vaginal patency). An increase in the percentage of male offspring was also observed in litters from offspring (F2 generation) exposed to maternal doses of 250 mg/kg/day. There were no effects on natural delivery in mice treated with 1.2 times (30 mg/kg/day) the expected systemic exposure at the MRHD.

8.2 Lactation

Risk Summary

There is no information on the presence of solifenacin in human milk, the effects on the breastfed child, or the effects on milk production. Solifenacin is present in mouse milk [see Data]. When a drug is present in animal milk, it is likely that the drug will be present in human milk. The developmental and health benefits of breastfeeding should be considered along with the mother’s clinical need for VESIcare LS and any potential adverse effects on the breastfed child from VESIcare LS or from the underlying maternal condition.

Data

Animal Data

Oral administration of ^14C-solifenacin succinate to lactating mice resulted in the recovery of radioactivity in maternal milk. Lactating female mice orally administered solifenacin succinate at a maternally toxic dose of 100 mg/kg/day (3.6 times the systemic exposure at the MRHD) had increased postpartum pup mortality, pups with reduced body weights, or delays in the onset of reflex and physical development. Pups from lactating dams orally administered solifenacin succinate at a dose of 30 mg/kg/day (1.2 times the systemic exposure at the MRHD) had no discernible adverse findings. The concentrations of solifenacin in animal milk does not necessarily predict the concentration of drug in human milk.

8.4 Pediatric Use

The safety and effectiveness of VESIcare LS have been established in pediatric patients aged 2 years and older for the treatment of neurogenic detrusor overactivity (NDO) and the information on this use is discussed throughout the labeling. The safety and effectiveness of VESIcare LS have not been established in pediatric patients less than 2 years of age.

8.6 Renal Impairment

Solifenacin plasma concentrations are greater in adults with severe renal impairment compared to adults with normal renal function [see Clinical Pharmacology (12.3)]. Because increased solifenacin plasma concentrations increase the risk of antimuscarinic adverse reactions, the maximum recommended dose of VESIcare LS oral suspension in pediatric patients 2 years of age and older with severe renal impairment (CLcr < 30 mL/min/1.73 m^2) is the starting dose [see Dosage and Administration (2.2)]. The recommended dose in patients with mild or moderate renal impairment is the same as in patients with normal renal function.

8.7 Hepatic Impairment

Solifenacin plasma concentrations are greater in adults with moderate hepatic impairment compared to adults with normal hepatic function [see Clinical Pharmacology (12.3)]. Because increased solifenacin plasma concentrations increase the risk of antimuscarinic adverse reactions, the maximum recommended dose of VESIcare LS oral suspension in pediatric patients 2 years of age and older with moderate hepatic impairment (Child-Pugh B) is the starting dose [see Dosage and Administration (2.3)] and VESIcare LS oral suspension is not recommended for use in patients with severe hepatic impairment (Child-Pugh C).

10 OVERDOSAGE

Overdosage with VESIcare LS oral suspension can potentially result in severe antimuscarinic effects and should be treated accordingly. The highest dose ingested in an accidental overdose of solifenacin succinate was 280 mg (28 times the maximum dosage) in a 5-hour period in adults. This case was associated with mental status changes. Some cases reported a decrease in the level of consciousness.

Intolerable antimuscarinic adverse reactions (fixed and dilated pupils, blurred vision, failure of heel-to-toe exam, tremors, and dry skin) occurred on day 3 in normal adult volunteers taking 50 mg daily (5 times the maximum recommended dosage) and resolved within 7 days following discontinuation of drug.

The highest overdose reported in a pediatric patient was the accidental ingestion of 95 mg of solifenacin succinate (9.5 times the maximum recommended dosage). The child experienced severe antimuscarinic adverse reactions and was treated with gastric lavage and supportive measures until all antimuscarinic signs and symptoms reversed.

In the event of overdose with VESIcare LS oral suspension, treat with gastric lavage and appropriate supportive measures. ECG monitoring is also recommended.

11 DESCRIPTION

VESIcare LS (solifenacin succinate) oral suspension is a muscarinic receptor antagonist. Chemically, solifenacin succinate is a butanedioic acid compound with (1S)-(3R)-1-azabicyclo[2.2.2]oct-3-yl 3,4-dihydro-1-phenyl-2(1H)-iso-quinolinecarboxylate (1:1) having an empirical formula of C23H26N2O2•C4H6O4, and a molecular weight of 480.55. The structural formula of solifenacin succinate is:

Solifenacin succinate is a white to pale-yellowish-white crystal or crystalline powder. It is freely soluble at room temperature in water, glacial acetic acid, dimethyl sulfoxide, and methanol.

VESIcare LS contains 1 mg/mL of solifenacin succinate as an oral suspension (1 mg solifenacin succinate is equivalent to 0.75 mg solifenacin). The inactive ingredients are polacrilin potassium, methylparaben, propylparaben, propylene glycol, simethicone emulsion 30%, carbomer homopolymer Type B, xylitol, acesulfame potassium, natural orange flavor, sodium hydroxide, and purified water. VESIcare LS is a white to off-white color aqueous homogenous oral suspension with an orange flavor.

12 CLINICAL PHARMACOLOGY

12.1 Mechanism of Action

Solifenacin is a competitive muscarinic receptor antagonist. Muscarinic receptors play an important role in several major cholinergically mediated functions, including contractions of urinary bladder smooth muscle.

12.2 Pharmacodynamics

Cardiac Electrophysiology

The effect of 10 mg and 30 mg solifenacin succinate (three times the maximum recommended dose) on the QT interval was evaluated in adults at the time of peak plasma concentration of solifenacin in a multi-dose, randomized, double-blind, placebo and positive-controlled (moxifloxacin 400 mg) trial [see Warnings and Precautions (5.6)]. After receiving placebo and moxifloxacin sequentially, adult subjects were randomized to one of two treatment groups. One group (n=51) completed 3 additional sequential periods of dosing with solifenacin succinate 10, 20, and 30 mg while the second group (n=25) in parallel completed a sequence of placebo and moxifloxacin. Study subjects were female volunteers aged 19 to 79 years. The 30 mg dose of solifenacin succinate (three times the highest recommended dose) was chosen for use in this study because this dose results in a solifenacin exposure that covers those observed upon coadministration of 10 mg solifenacin succinate with strong CYP3A4 inhibitors (e.g., ketoconazole, 400 mg). Due to the sequential dose escalating nature of the study, baseline ECG measurements were separated from the final QT assessment (of the 30 mg dose level) by 33 days.

The median difference from baseline in heart rate associated with the 10 and 30 mg doses of solifenacin succinate compared to placebo was -2 and 0 beats/minute, respectively. Because a significant period effect on QTc was observed, the QTc effects were analyzed utilizing the parallel placebo control arm rather than the pre-specified intra-patient analysis. Representative results are shown in Table 3.

Table 3: QTc changes in msec (90% CI) from baseline at Tmax (relative to placebo) in adults [Results displayed are those derived from the parallel design portion of the study and represent the comparison of Group 1 to time-matched placebo effects in Group 2.]
Drug/Dose | Fridericia Method (using mean difference)
Solifenacin succinate 10 mg | 2 (-3, 6)
Solifenacin succinate 30 mg | 8 (4, 13)

Moxifloxacin was included as a positive control in this study and, given the length of the study, its effect on the QT interval was evaluated in 3 different sessions. The placebo-subtracted mean changes (90% CI) in QTcF for moxifloxacin in the three sessions were 11 (7, 14), 12 (8, 17), and 16 (12, 21), respectively.

The QT interval prolonging effect of the highest solifenacin succinate dose (three times the maximum therapeutic dose) studied was not as large as that of the positive control moxifloxacin at its recommended dose. However, the confidence intervals overlapped, and this study was not designed to draw direct statistical conclusions between the drugs or the dose levels.

12.3 Pharmacokinetics

Absorption

After oral administration of VESIcare LS in pediatric patients with neurogenic detrusor overactivity (NDO) aged 2 to 17 years, peak plasma concentrations (Cmax) of solifenacin were reached within 2 to 6 hours after administration (tmax) and, at steady-state, the dose-normalized Cmax ranged from 2.5 - 29 ng/mL/mg. The absolute bioavailability of solifenacin in adults is approximately 90%, with plasma concentrations of solifenacin proportional to the dose administered.

Effect of Food
Food intake did not significantly affect the Cmax and AUC of solifenacin following oral administration of VESIcare LS.

Distribution

Solifenacin is approximately 98% (in vivo) bound to human plasma proteins, principally to α1-acid glycoprotein. Solifenacin is highly distributed to non-CNS tissues, having a median steady-state volume of distribution of 211 L in pediatric neurogenic detrusor overactivity (NDO) patients from 2 to 17 years old.

Elimination

The median elimination half-life of solifenacin is approximately 26 hours in pediatric neurogenic detrusor overactivity (NDO) patients 2 years of age and older.

Metabolism
Solifenacin is extensively metabolized in the liver. The primary pathway for elimination is by way of CYP3A4; however, alternate metabolic pathways exist. The primary metabolic routes of solifenacin are through N-oxidation of the quinuclidin ring and 4R-hydroxylation of the tetrahydroisoquinoline ring. One pharmacologically active metabolite (4R-hydroxy solifenacin), occurring at low concentrations and unlikely to contribute significantly to clinical activity, and three pharmacologically inactive metabolites (N-glucuronide and the N-oxide and 4R-hydroxy-N-oxide of solifenacin) have been found in human plasma after oral dosing.
Excretion
Following the administration of 10 mg of ^14C-solifenacin succinate to healthy adult volunteers, 69% of the radioactivity was recovered in the urine and 23% in the feces over 26 days. Less than 15% (as mean value) of the dose was recovered in the urine as intact solifenacin. The major metabolites identified in urine were N-oxide of solifenacin, 4R-hydroxy solifenacin, and 4R-hydroxy-N-oxide of solifenacin and, in feces, 4R-hydroxy solifenacin.

Specific Populations

Patients with Renal Impairment
In studies with solifenacin succinate 10 mg in adults, there was a 2.1-fold increase in AUC and a 1.6-fold increase in t1/2 of solifenacin in patients with severe renal impairment compared to subjects with normal renal function [see Use in Specific Populations (8.6)].
Patients with Hepatic Impairment
In studies with solifenacin succinate 10 mg in adults, there was a 2-fold increase in the t1/2 and a 35% increase in AUC of solifenacin in patients with moderate hepatic impairment compared to subjects with normal hepatic function [see Use in Specific Populations (8.7)]. Solifenacin succinate has not been studied in patients with severe hepatic impairment.

Drug Interaction Studies

Interaction studies have only been performed in adults. In pediatric patients 2 years of age and older, metabolism via CYP3A4 is the major route of elimination and the metabolic capacity of the liver is similar.

Strong CYP3A4 Inhibitors
In a crossover study in adults, following blockade of CYP3A4 by coadministration of the strong CYP3A4 inhibitor, ketoconazole 400 mg once daily for 21 days, the mean Cmax and AUC of solifenacin increased by 1.5 and 2.7-fold, respectively [see Dosage and Administration (2.4) and Drug Interactions (7.1)].
CYP3A4 Inducers
Because solifenacin is a substrate of CYP3A4, inducers of CYP3A4 may decrease the concentration of solifenacin.
Warfarin
In a crossover study in adults, subjects received a single oral dose of warfarin 25 mg on the 10th day of dosing with either solifenacin succinate 10 mg or matching placebo once daily for 16 days. For R-warfarin, when it was coadministered with solifenacin succinate, the mean Cmax increased by 3% and AUC decreased by 2%. For S-warfarin, when it was coadministered with solifenacin succinate, the mean Cmax and AUC increased by 5% and 1%, respectively.
Oral Contraceptives
In a crossover study in adults, subjects received 2 cycles of 21 days of oral contraceptives containing 30 ug ethinyl estradiol and 150 ug levonorgestrel. During the second cycle, subjects received additional solifenacin succinate 10 mg or matching placebo once daily for 10 days starting from the 12th day of receipt of oral contraceptives. For ethinyl estradiol, when it was administered with solifenacin succinate, the mean Cmax and AUC increased by 2% and 3%, respectively. For levonorgestrel, when it was administered with solifenacin succinate, the mean Cmax and AUC decreased by 1%.
Digoxin
In a crossover study in adults, subjects received digoxin (loading dose of 0.25 mg on day 1, followed by 0.125 mg from days 2 to 8) for 8 days. Consecutively, they received solifenacin succinate 10 mg or matching placebo with digoxin 0.125 mg for an additional 10 days. When digoxin was coadministered with solifenacin succinate, the mean Cmax and AUC increased by 13% and 4%, respectively.
Drugs Metabolized by Cytochrome P450 Enzymes
  In vitro studies demonstrated that, at therapeutic concentrations, solifenacin does not inhibit CYP1A1/2, 2C9, 2C19, 2D6, or 3A4 derived from human liver microsomes.

13 NONCLINICAL TOXICOLOGY

13.1 Carcinogenesis, Mutagenesis, Impairment of Fertility

No increase in tumors was found following the administration of solifenacin succinate to male and female mice for 104 weeks at doses up to 200 mg/kg/day (5 and 9 times, respectively, of the exposure at the maximum recommended human dose [MRHD] of 10 mg), and male and female rats for 104 weeks at doses up to 20 and 15 mg/kg/day, respectively (< 1 times the exposure at the MRHD).

Solifenacin succinate was not mutagenic in the in vitro Salmonella typhimurium or Escherichia coli microbial mutagenicity test or chromosomal aberration test in human peripheral blood lymphocytes with or without metabolic activation or in the in vivo micronucleus test in rats.

Solifenacin succinate had no effect on reproductive function, fertility, or early embryonic development of the fetus in male and female mice treated with 250 mg/kg/day (13 times the exposure at the MRHD) of solifenacin succinate, and in male rats treated with 50 mg/kg/day (< 1 times the exposure at the MRHD) and female rats treated with 100 mg/kg/day (1.7 times the exposure at the MRHD) of solifenacin succinate.

13.2 Animal Toxicology and/or Pharmacology

Juvenile Animal Toxicology Data

Dose-related increased mortality without preceding clinical signs occurred in juvenile mice treated before weaning for a duration of 12 weeks, from day 10 after birth, with doses that achieved a pharmacological effect. Animals dosed from postnatal day 10 onwards had higher mortality compared to the mortality in adult mice. No increased frequency in mortality was observed in juvenile mice that were treated after weaning for a duration of 4 weeks, from day 21 after birth onwards. Plasma exposure at postnatal day 10 was higher than in adult mice; the systemic exposure at postnatal day 21 was comparable to the systemic exposure in adult mice.

14 CLINICAL STUDIES

The efficacy of VESIcare LS oral suspension was evaluated in two 52-week, open-label, baseline-controlled, sequential dose titration studies in a total of 95 pediatric patients 2 years of age and older with neurogenic detrusor overactivity (NDO). Study 1 (NCT01981954) included patients 2 to less than 5 years of age and Study 2 (NCT01565694) included patients 5 to 17 years of age. Entry criteria required that patients had a diagnosis of neurogenic detrusor overactivity (NDO) confirmed by urodynamics demonstrating the presence of involuntary detrusor contractions with detrusor pressure increase greater than 15 cm H2O and that patients or their caregivers practiced clean intermittent catheterization (CIC). VESIcare LS oral suspension was administered once daily. All patients initially received a weight-based starting dose, followed by dose titration to their lowest effective dose, up to a maximum dose. The duration of the dose titration period was up to 12 weeks and this period was followed by a dose maintenance period of at least 40 weeks.

In Study 1, a total of 19 patients aged 2 to less than 5 years of age received VESIcare LS oral suspension. Of these, 17 patients completed treatment through week 24 and had adequate urodynamic measurements for evaluation of efficacy. The optimized maintenance dose within this study population included 63% of patients at the maximum dose, 26% of patients at an intermediate dose, and 5% of patients at the starting dose. The study population included 7 males (41%) and 10 females (59%).

In Study 2, a total of 76 patients aged 5 to 17 years of age received VESIcare LS oral suspension. Of these, 49 patients (24 patients aged 5 to < 12 years and 25 patients aged 12 to 17 years) completed treatment through week 24 and had adequate urodynamic measurements for evaluation of efficacy. The optimized maintenance dose within this study population included 58% of patients at the maximum dose, 15% of patients at an intermediate dose, and 7% of patients at the starting dose. This study population included 24 males (49%) and 25 females (51%).

The primary efficacy endpoint was change from baseline in the patients’ maximum cystometric (bladder) capacity (MCC) after 24 weeks of treatment with VESIcare LS oral suspension. As shown in Table 4, an improvement in MCC was observed in patients aged 2 to less than 5 years of age and in patients aged 5 to 17 years of age. The magnitude of the observed changes from baseline in the primary and secondary efficacy endpoints were comparable between patients 5 to less than 12 years of age and patients 12 to 17 years of age.

The results for the primary efficacy endpoint in the 2 clinical studies of VESIcare LS oral suspension in pediatric patients with neurogenic detrusor overactivity (NDO) are shown in Table 4. Treatment effects were maintained over 52 weeks.

Table 4: Change from Baseline in Maximum Cystometric Capacity (MCC) at 24 Weeks in Pediatric Patients with Neurogenic Detrusor Overactivity (NDO) Treated with VESIcare LS Oral Suspension in Studies 1 and 2
 | Aged 2 to Less than 5 Years (N=17) Mean (SD) | Aged 5 to 17 Years (N=49) Mean (SD)
Maximum Cystometric Capacity (mL)
Baseline; Week 24; Change from baseline | 98 (40); 137 (37); 39 (36); 95% CI: 21, 57 | 224 (133) [Baseline values for patients aged 5 to 17 years are based on patients who took at least one dose and provided valid baseline and at least one post-baseline values for MCC.]; 279 (127); 57 (108); 95% CI: 26, 88
N is the number of patients who took at least one dose and provided valid values for MCC at baseline and Week 24.

Results for other urodynamic parameters and from patient urinary diaries, which were secondary efficacy endpoints in Studies 1 and 2, are shown in Tables 5 and 6, respectively.

Table 5: Changes from Baseline in Other Urodynamic Parameters at Week 24 in Pediatric Patients with Neurogenic Detrusor Overactivity (NDO) Treated with VESIcare LS Oral Suspension in Studies 1 and 2
 | Aged 2 to Less than 5 Years; (N=17); Mean (SD) | Aged 5 to 17 Years; (N=49); Mean (SD)
Bladder Compliance (mL/cm H2O); Baseline; Change from baseline | 5.7 (4.9); 5.8 (7.3); 95% CI: 2.2, 9.6 | 14.6 (36.4) [Baseline values for patients aged 5 to 17 years are based on patients who took at least one dose and provided valid baseline and at least one post-baseline values for MCC.]; 9.1 (28.6); 95% CI: 1.0, 17.2
Number of Overactive Detrusor Contractions; (> 15 cm H2O); Baseline; Change from baseline | 9.9 (11.6); -7.0 (9.3); 95% CI: -11.8, -2.2 | 3.9 (4.7); -2.3 (5.1); 95% CI: -3.7, -0.8
Percentage of Expected Bladder Volume Prior To First Detrusor Contraction > 15 cm H2O [For patients who showed a detrusor contraction during the urodynamic assessment at Week 24.]; Baseline (median); Change from baseline (median) | 15.8%; 31.1% | 27.7%; 13.3%
N is the number of patients who took at least one dose and provided valid values for MCC at baseline and Week 24.

Table 6: Changes from Baseline in Maximum Catheterized Urine Volume and Number of Incontinence Episodes at Week 24 in Pediatric Patients with Neurogenic Detrusor Overactivity (NDO) Treated with VESIcare LS Oral Suspension in Studies 1 and 2
 | Aged 2 to Less than 5 Years; (N=17) | Aged 5 to 17 Years; (N=49)
Maximum Catheterized Urine Volume/Day (mL); Baseline; Change from baseline | 77 (43.0); 45 (54.7); 95% CI: 15, 76 | 204 (92.7); 68 (88.1); 95% CI: 43, 92
Number of Incontinence Episodes/24 hours [For patients aged 2 to less than 5 years, the number of incontinence episodes per 24 hours was evaluated as the number of periods between clean intermittent catheterizations with incontinence per 24 hours.]; Baseline; Change from baseline | 3.9 (0.8); -1.6 (1.2); 95% CI: -2.3, -0.9 | 3.4 (2.9); -1.6 (2.0); 95% CI: -2.2, -1.0

16 HOW SUPPLIED/STORAGE AND HANDLING

VESIcare LS is supplied as a white to off-white colored 5 mg/5 mL (1 mg/mL) aqueous oral suspension of solifenacin succinate, packaged in 150 mL amber polyethylene terephthalate (PET) bottles, which are capped with child-resistant high-density polyethylene-polypropylene caps with a pulp and vinyl seal liner.

Carton contains one bottle (NDC 51248-250-99)

Store at 20°C to 25°C (68°F to 77°F) with excursions permitted from 15°C to 30°C (59°F to 86°F) [see USP Controlled Room Temperature]. Store in original bottle to protect from degradation. Dispense in a tight, light-resistant container. Discard any unused product 28 days after opening the original bottle.

17 PATIENT COUNSELING INFORMATION

Advise the patient and/or caregiver to read the FDA-approved patient labeling (Patient Information).

Angioedema and Anaphylactic Reactions

Inform patients and/or their caregivers that angioedema and anaphylactic reactions have been reported in patients treated with solifenacin succinate. Angioedema and anaphylactic reactions may be life-threatening. Advise patients to promptly discontinue VESIcare LS therapy and seek immediate attention if they experience edema of the tongue or laryngopharynx, or difficulty breathing [see Contraindications (4) and Warnings and Precautions (5.1)].

Urinary Retention

Inform patients and/or their caregivers that VESIcare LS may cause urinary retention in patients with conditions associated with bladder outlet obstruction [see Warnings and Precautions (5.2)].

Gastrointestinal Disorders

Inform patients and/or their caregivers that VESIcare LS oral suspension may cause further decrease in gastrointestinal motility in patients with conditions associated with decreased gastrointestinal motility. VESIcare LS oral suspension has been associated with constipation and dry mouth. Advise patients and/or their caregivers to contact their health care providers if they experience severe abdominal pain or become constipated for 3 or more days [see Warnings and Precautions (5.3)].

Central Nervous System Effects

Because VESIcare LS oral suspension, like other antimuscarinic agents, may cause central nervous system effects or blurred vision, advise patients and/or caregivers to exercise caution in decisions to engage in potentially dangerous activities until the drug’s effect on the patient has been determined [see Warnings and Precautions (5.4)].

Narrow-Angle Glaucoma

Inform patients and/or caregivers that VESIcare LS, like other antimuscarinics, may cause worsening of the glaucoma condition in patients with narrow-angle glaucoma [see Warnings and Precautions (5.5)].

Dry Skin

Inform patients and/or caregivers that VESIcare LS, like other antimuscarinics, may cause dry skin due to decreased sweating. Heat prostration due to decreased sweating can occur when antimuscarinic drugs are used in a hot environment [see Adverse Reactions (6.2)].

Administration Instructions

Ensure that the patient has an appropriate measuring device and instructions for measuring the correct dose. Instruct patients or their caregivers to use an oral dosing syringe to correctly measure the prescribed amount of VESIcare LS oral suspension. Inform patients that oral dosing syringes may be obtained from their pharmacy. Instruct patients or their caregivers to shake the bottle well prior to administration of each dose and that patients should take VESIcare LS orally followed by liquid (e.g., water or milk) 1 time a day. Inform patients or their caregivers that simultaneous use of VESIcare LS oral suspension with food and/or other liquids may result in a bitter taste.

- Clean the measuring device and allow to dry after each use.
- Discard VESIcare LS 28 days (4 weeks) after first opening the bottle.

Instruct patients or their caregivers that patients should take VESIcare LS orally followed by liquid (e.g., water or milk). Instruct patients to take any missed doses as soon as they remember, unless more than 12 hours have passed since the missed dose. If more than 12 hours have passed, the missed dose can be skipped and the next dose should be taken at the usual time.

Marketed and Distributed by:
Astellas Pharma US, Inc.
Northbrook, IL 60062

VESIcare LS is a registered trademark of Astellas US LLC.
© 2004 – 2022 Astellas Pharma US, Inc.
366572-VES

Patient Information

VESIcare LS® (VES-ih-care LS)

(solifenacin succinate)

oral suspension

What is VESIcare LS?

- VESIcare LS is a prescription medicine for children aged 2 years of age and older with a condition called neurogenic detrusor overactivity. It is used to increase the amount of urine your bladder can hold and reduce urine leakage.

Who should not take VESIcare LS?

Do not take VESIcare LS if you:

- have delayed or slow emptying of your stomach (gastric retention).
- have an eye problem called “uncontrolled narrow-angle glaucoma”.
- are allergic to solifenacin succinate or any of the ingredients in VESIcare LS. See the end of this leaflet for a complete list of ingredients.

Before you take VESIcare LS, tell your doctor if you have any medical conditions, including if you:

- have any stomach or intestinal problems or problems with constipation.
- have trouble emptying your bladder or you have a weak urine stream.
- have liver problems.
- have kidney problems.
- have a heart problem called “QT prolongation”.
- are pregnant or plan to become pregnant. It is not known if VESIcare LS will harm your unborn baby. Talk to your doctor if you are pregnant or plan to become pregnant.
- are breastfeeding or plan to breastfeed. It is not known if VESIcare LS passes into your breast milk. Talk to your doctor about the best way to feed your baby if you take VESIcare LS.

Tell your doctor about all the medicines you take, including prescription and over-the-counter medicines, vitamins, and herbal supplements. VESIcare LS may affect the way other medicines work, and other medicines may affect how VESIcare LS works.

How should I take VESIcare LS?

- Take VESIcare LS exactly as your doctor tells you to take it.
- If you have questions about dosing, talk to your pharmacist for instructions on how to prepare and administer VESIcare LS.
- Shake the bottle well before taking each dose.
- You should take VESIcare LS by mouth 1 time a day.
- Use an oral dosing device, such as an oral syringe, to correctly measure your dose. Ask your pharmacist for an appropriate oral dosing device.
- You should take VESIcare LS followed by water or milk. Avoid taking VESIcare LS at the same time with food or other drinks, as this may result in a bitter taste.
- Do not take 2 doses of VESIcare LS the same day. If you miss a dose of VESIcare LS, take it as soon as possible. If it has been 12 hours since taking the last dose of VESIcare LS, skip that dose and take the next dose at the usual time.
- If you take too much VESIcare LS, call your doctor or go to the nearest hospital emergency room right away.

What should I avoid while taking VESIcare LS?

VESIcare LS can cause blurred vision or drowsiness. Do not drive or operate heavy machinery until you know how VESIcare LS affects you.

What are the possible side effects of VESIcare LS?

VESIcare LS may cause serious side effects including:

- Serious allergic reaction. Stop taking VESIcare LS and get medical help right away if you have:
  - hives, skin rash, or swelling
  - severe itching
  - swelling of your face, mouth, or tongue
  - trouble breathing
- Central Nervous System (CNS) effects. Talk to your doctor right away if you get any of these side effects:
  - headache
  - confusion
  - hear voices, see things, or sense things that are not there (hallucinations)
  - sleepiness

The most common side effects of VESIcare LS include:

- constipation. Call your doctor if you get severe stomach area (abdominal) pain or become constipated for 3 or more days.
- dry mouth
- urinary tract infection

Other side effects have been observed with anticholinergic medicines such as VESIcare LS and may include:

- blurred vision
- dry eyes
- dry skin due to decreased sweating. Heat exhaustion or heat stroke due to decreased sweating can happen when anticholinergic medications such as VESIcare LS are used in hot environments. Symptoms may include:
  - decreased sweating
  - dizziness
  - tiredness
  - nausea
  - increase in body temperature

Tell your doctor if you have any side effect that bothers you or that does not go away.

These are not all the possible side effects of VESIcare LS. For more information, ask your doctor or pharmacist.

Call your doctor for medical advice about side effects. You may report side effects to FDA at 1-800-FDA-1088.

How should I store VESIcare LS?

- Store VESIcare LS at room temperature, between 68°F to 77°F (20°C to 25°C) with the cap closed.
- Store VESIcare LS in the original bottle.
- Throw away VESIcare LS oral suspension 28 days (4 weeks) after first opening.
- Safely throw away VESIcare LS that has expired or is unused.

Keep VESIcare LS and all medicines out of the reach of children.

General information about the safe and effective use of VESIcare LS.

Medicines are sometimes prescribed for purposes other than those listed in a Patient Information leaflet. Do not use VESIcare LS for a condition for which it was not prescribed. Do not give VESIcare LS to other people, even if they have the same symptoms you have. It may harm them.

This leaflet summarizes the most important information about VESIcare LS. If you would like more information, talk with your doctor. You can ask your doctor or pharmacist for information about VESIcare LS that is written for health professionals.

What are the ingredients in VESIcare LS?

Active ingredient: solifenacin succinate

Inactive ingredients: polacrilin potassium, methylparaben, propylparaben, propylene glycol, simethicone emulsion 30%, carbomer homopolymer Type B, xylitol, acesulfame potassium, natural orange flavor, sodium hydroxide, and purified water.

Marketed and Distributed by:

Astellas Pharma US, Inc.

Northbrook, IL 60062
VESIcare LS is a registered trademark of Astellas US LLC.
© 2004 – 2022 Astellas Pharma US, Inc.
For more information, call 1-800-727-7003.
366572-VES

This Patient Information has been approved by the U.S. Food and Drug Administration. Revised: 10/2022

PACKAGE/LABEL PRINCIPAL DISPLAY PANEL

NDC 51248-250-99

VESIcare LS®

(solifenacin succinate)

Oral Suspension

5 mg/5 mL

(1 mg/mL)

Shake the bottle well before use.

Discard remaining VESIcare LS® 28 days after first opening.

150 mL

Package/Label Display Panel

NDC 51248-250-99

VESIcare LS®

(solifenacin succinate)

Oral Suspension

5 mg/5 mL

(1 mg/mL)

Rx only

Shake well before use.

150 mL